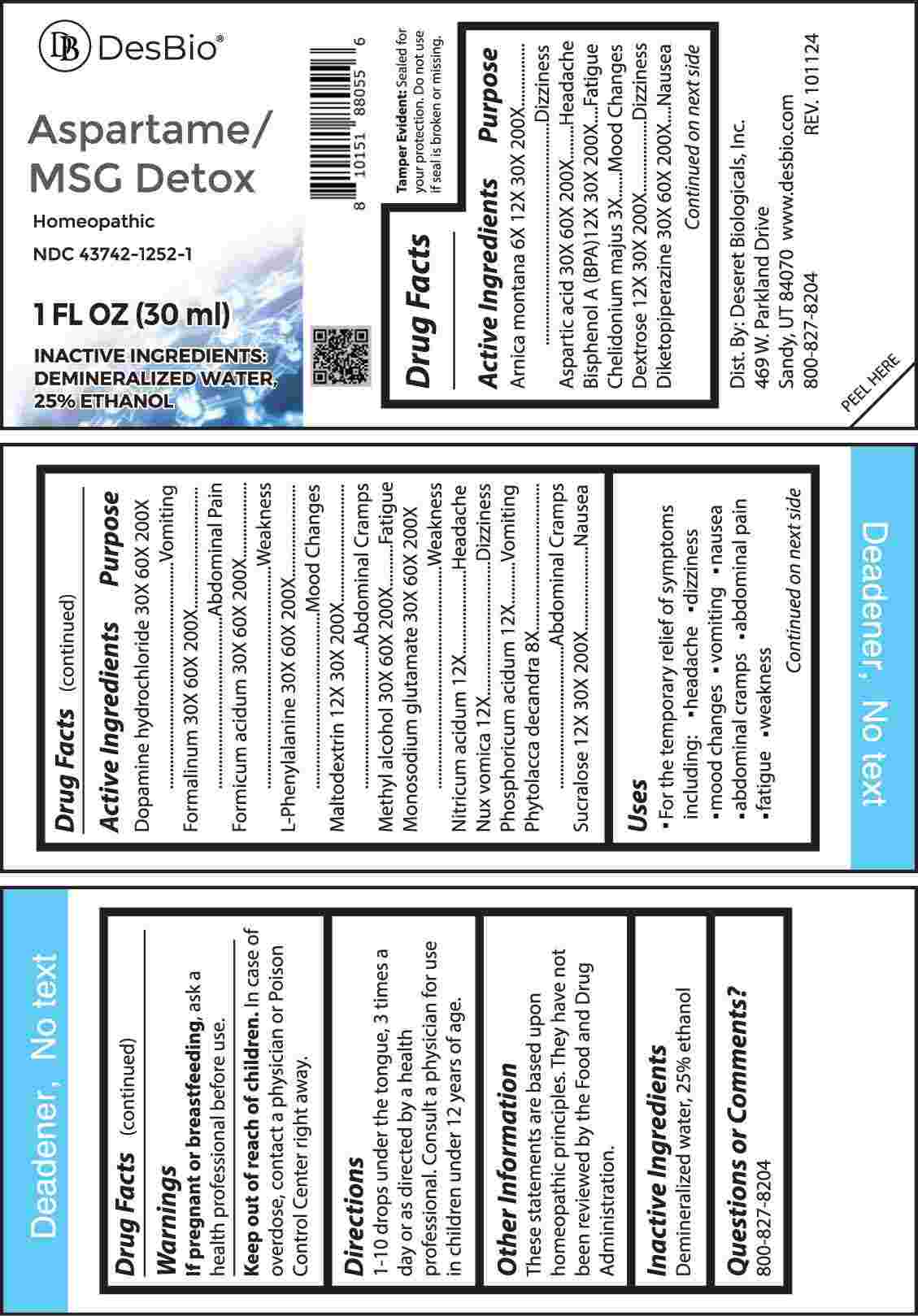 DRUG LABEL: Aspartame/MSG Detox
NDC: 43742-1252 | Form: LIQUID
Manufacturer: Deseret Biologicals, Inc.
Category: homeopathic | Type: HUMAN OTC DRUG LABEL
Date: 20250311

ACTIVE INGREDIENTS: CHELIDONIUM MAJUS WHOLE 3 [hp_X]/1 mL; ARNICA MONTANA WHOLE 6 [hp_X]/1 mL; PHYTOLACCA AMERICANA ROOT 8 [hp_X]/1 mL; NITRIC ACID 12 [hp_X]/1 mL; STRYCHNOS NUX-VOMICA SEED 12 [hp_X]/1 mL; PHOSPHORIC ACID 12 [hp_X]/1 mL; BISPHENOL A 12 [hp_X]/1 mL; DEXTROSE MONOHYDRATE 12 [hp_X]/1 mL; MALTODEXTRIN 12 [hp_X]/1 mL; SUCRALOSE 12 [hp_X]/1 mL; ASPARTIC ACID 30 [hp_X]/1 mL; 2,5-PIPERAZINEDIONE 30 [hp_X]/1 mL; DOPAMINE HYDROCHLORIDE 30 [hp_X]/1 mL; FORMALDEHYDE 30 [hp_X]/1 mL; FORMIC ACID 30 [hp_X]/1 mL; METHYL ALCOHOL 30 [hp_X]/1 mL; MONOSODIUM GLUTAMATE 30 [hp_X]/1 mL; PHENYLALANINE 30 [hp_X]/1 mL
INACTIVE INGREDIENTS: WATER; ALCOHOL

DRUG FACTS:

ACTIVE INGREDIENTS:

Arnica Montana 6X, 12X, 30X, 200X, Aspartic Acid 30X, 60X, 200X, Bisphenol A (BPA) 12X, 30X, 200X, Chelidonium Majus 3X, Dextrose 12X, 30X, 200X, Diketopiperazine 30X, 60X, 200X, Dopamine Hydrochloride 30X, 60X, 200X, Formalinum 30X, 60X, 200X, Formicum Acidum 30X, 60X, 200X, L-Phenylalanine 30X, 60X, 200X, Maltodextrin 12X, 30X, 200X, Methyl Alcohol 30X, 60X, 200X, Monosodium Glutamate 30X, 60X, 200X, Nitricum Acidum 12X, Nux Vomica 12X, Phosphoricum Acidum 12X, Phytolacca Decandra 8X, Sucralose 12X, 30X, 200X.

PURPOSE:

Arnica Montana - Dizziness, Aspartic Acid - Headache, Bisphenol A (BPA) - Fatigue, Chelidonium Majus – Mood Changes, Dextrose - Dizziness, Diketopiperazine - Nausea, Dopamine Hydrochloride - Vomiting, Formalinum – Abdominal Pain, Formicum Acidum - Weakness, L-Phenylalanine – Mood Changes, Maltodextrin – Abdominal Cramps, Methyl Alcohol - Fatigue, Monosodium Glutamate - Weakness, Nitricum Acidum – Headache, Nux Vomica - Dizziness, Phosphoricum Acidum - Vomiting, Phytolacca Decandra – Abdominal Cramps, Sucralose - Nausea

USES:

• For the temporary relief of symptoms including:

• headache • dizziness • mood changes • vomiting • nausea

• abdominal cramps • abdominal pain • fatigue • weakness

These statements are based upon homeopathic principles. They have not been reviewed by the Food and Drug Administration.

WARNINGS:

If pregnant or breastfeeding, ask a health professional before use.

Keep out of reach of children. In case of overdose, contact a physician or Poison Control Center right away.

Tamper Evident: Sealed for your protection. Do not use if seal is broken or missing.

KEEP OUT OF REACH OF CHILDREN:

In case of overdose, contact a physician or Poison Control Center right away.

DIRECTIONS:

1-10 drops under the tongue, 3 times a day or as directed by a health professional. Consult a physician for use in children under 12 years of age.

INACTIVE INGREDIENTS:

Demineralized water, 25% ethanol

QUESTIONS:

Dist. By: Deseret Biologicals, Inc.
469 W. Parkland Drive
Sandy, UT 84070

www.desbio.com

800-827-8204

PACKAGE LABEL DISPLAY:

Des Bio

Aspartame/MSG Detox

Homeopathic

NDC 43742-1252-1

1 FL OZ (30 ml)